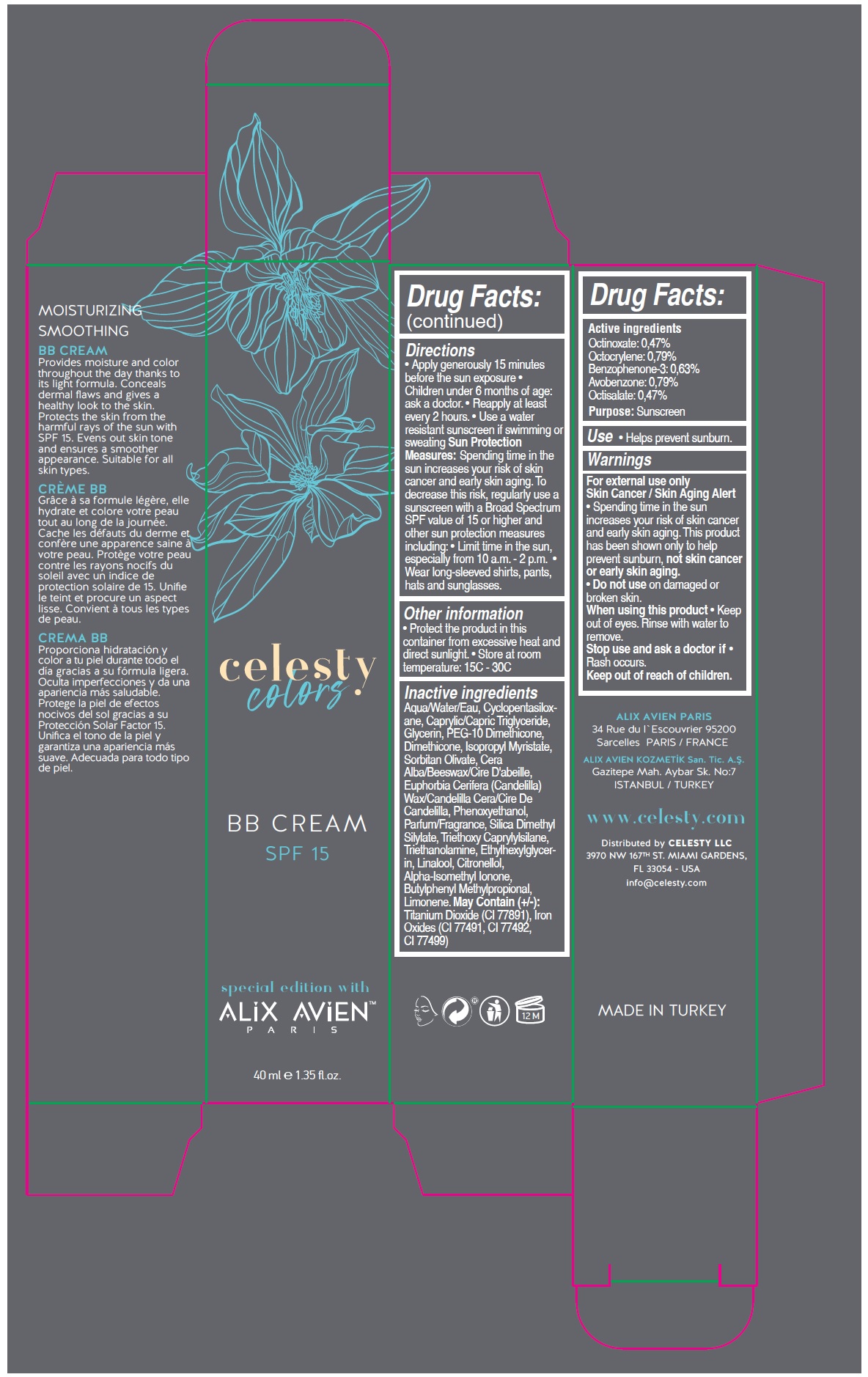 DRUG LABEL: Celesty Colors Special Edition With Alix Avien
NDC: 81120-116 | Form: CREAM
Manufacturer: MABA KOZMETIK LIMITED SIRKETI
Category: otc | Type: HUMAN OTC DRUG LABEL
Date: 20210320

ACTIVE INGREDIENTS: OCTINOXATE 4.7 mg/1 mL; OCTOCRYLENE 7.9 mg/1 mL; OXYBENZONE 6.3 mg/1 mL; AVOBENZONE 7.9 mg/1 mL; OCTISALATE 4.7 mg/1 mL
INACTIVE INGREDIENTS: WATER; CYCLOMETHICONE 5; MEDIUM-CHAIN TRIGLYCERIDES; GLYCERIN; PEG-10 DIMETHICONE (600 CST); DIMETHICONE; ISOPROPYL MYRISTATE; SORBITAN OLIVATE; YELLOW WAX; CANDELILLA WAX; PHENOXYETHANOL; SILICA DIMETHYL SILYLATE; TRIETHOXYCAPRYLYLSILANE; TROLAMINE; ETHYLHEXYLGLYCERIN; LINALOOL, (+/-)-; .BETA.-CITRONELLOL, (R)-; ISOMETHYL-.ALPHA.-IONONE; BUTYLPHENYL METHYLPROPIONAL; LIMONENE, (+)-; TITANIUM DIOXIDE; FERRIC OXIDE RED; FERRIC OXIDE YELLOW; FERROSOFERRIC OXIDE

Celesty colors special edition with ALIX AVIEN™ BB CREAM SPF 15

Active ingredients

Octinoxate: 0.47%
Octocrylene: 0.79%
Benzophenone-3: 0.63%
Avobenzone: 0.79%
Octisalate: 0.47%

Purpose:

Sunscreen

Use

• Helps prevent sunburn.

Warnings

For external use only

Skin Cancer / Skin Aging Alert
• Spending time in the sun increases your risk of skin cancer and early skin aging. This product has been shown only to help prevent sunburn, not skin cancer or early skin aging.

• Do not use on damaged or broken skin.

When using this product • Keep out of eyes. Rinse with water to remove.

Stop use and ask a doctor if • Rash occurs.

Keep out of reach of children.

Directions

• Apply generously 15 minutes before the sun exposure • Children under 6 months of age: ask a doctor. • Reapply at least every 2 hours. • Use a water resistant sunscreen if swimming or sweating Sun Protection Measures: Spending time in the sun increases your risk of skin cancer and early skin aging. To decrease this risk, regularly use a sunscreen with a Broad Spectrum SPF value of 15 or higher and other sun protection measures including: • Limit time in the sun, especially from 10 a.m. - 2 p.m. • Wear long-sleeved shirts, pants, hats and sunglasses.

Other information

• Protect the product in this container from excessive heat and direct sunlight. • Store at room temperature: 15C - 30C

Inactive ingredients

Aqua/Water/Eau, Cyclopentasiloxane, Caprylic/Capric Triglyceride, Glycerin, PEG-10 Dimethicone, Dimethicone, Isopropyl Myristate, Sorbitan Olivate, Cera Alba/Beeswax/Cire D'abeille, Euphorbia Cerifera (Candelilla) Wax/Candelilla Cera/Cire De Candelilla, Phenoxyethanol, Parfum/Fragrance, Silica Dimethyl Silylate, Triethoxy Caprylylsilane, Triethanolamine, Ethylhexylglycerin, Linalool, Citronellol, Alpha-Isomethyl Ionone, Butylphenyl Methylpropional, Limonene. May Contain (+/-): Titanium Dioxide (CI 77891), Iron Oxides (CI 77491, CI 77492, CI 77499)

BB CREAM

SPF 15

MOISTURIZING
SMOOTHING

Provides moisture and color throughout the day thanks to its light formula. Conceals dermal flaws and gives a healthy look to the skin. Protects the skin from the harmful rays of the sun with SPF 15. Evens out skin tone and ensures a smoother appearance. Suitable for all skin types.

ALIX AVIEN PARIS

34 Rue du l'Escouvrier 95200
Sarcelles PARIS / FRANCE

ALIX AVIEN KOZMETİK San. Tic. A.Ş.

Gazitepe Mah. Aybar Sk. No:7
ISTANBUL / TURKEY

www.celesty.com

Distributed by CELESTY LLC
3970 NW 167TH ST. MIAMI GARDENS,
FL 33054 - USA
info@celesty.com

MADE IN TURKEY